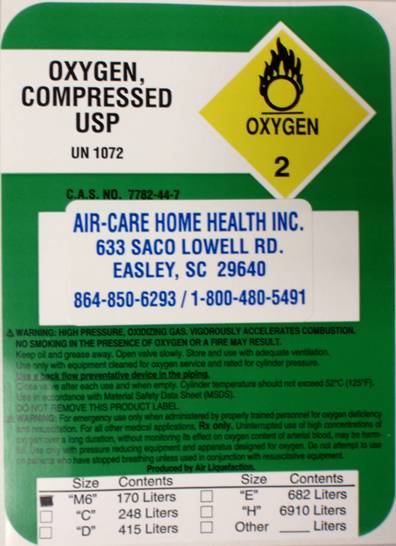 DRUG LABEL: Oxygen
NDC: 62737-123 | Form: GAS
Manufacturer: Air Care Home Health Inc
Category: prescription | Type: HUMAN PRESCRIPTION DRUG LABEL
Date: 20100825

ACTIVE INGREDIENTS: OXYGEN 1 L/1 L

PACKAGE LABEL

Oxygen